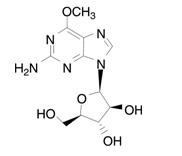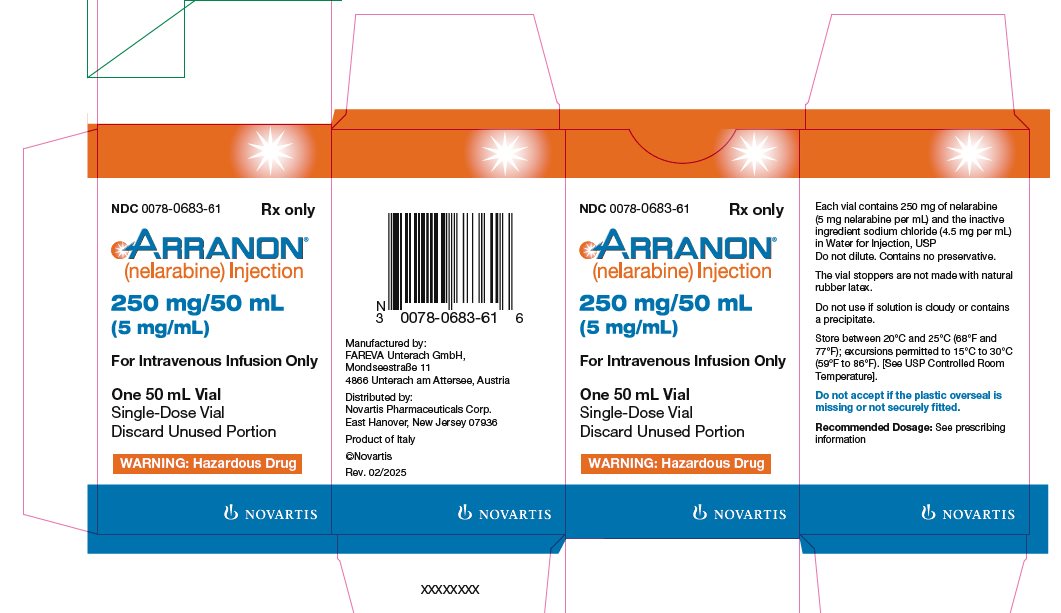 DRUG LABEL: Arranon
NDC: 0078-0683 | Form: INJECTION
Manufacturer: Novartis Pharmaceuticals Corporation
Category: prescription | Type: HUMAN PRESCRIPTION DRUG LABEL
Date: 20250331

ACTIVE INGREDIENTS: NELARABINE 5 mg/1 mL
INACTIVE INGREDIENTS: SODIUM CHLORIDE; WATER

HIGHLIGHTS OF PRESCRIBING INFORMATION

These highlights do not include all the information needed to use ARRANON safely and effectively. See full prescribing information for ARRANON.
ARRANON® (nelarabine) injection, for intravenous use
Initial U.S. Approval: 2005

WARNING: NEUROLOGIC ADVERSE REACTIONS

See full prescribing information for complete boxed warning.

Severe neurologic adverse reactions have been reported with the use of ARRANON. These adverse reactions have included altered mental states including severe somnolence, central nervous system effects including convulsions, and peripheral neuropathy ranging from numbness and paresthesias to motor weakness and paralysis. There have also been reports of adverse reactions associated with demyelination, and ascending peripheral neuropathies similar in appearance to Guillain-Barré syndrome. (5.1)

Full recovery from these adverse reactions has not always occurred with cessation of therapy with ARRANON. Monitor frequently for signs and symptoms of neurologic toxicity. Discontinue ARRANON for neurologic adverse reactions of NCI Common Toxicity Criteria for Adverse Events (CTCAE) Grade 2 or greater. (5.1)

1 INDICATIONS AND USAGE

ARRANON is a nucleoside metabolic inhibitor indicated for the treatment of patients with T-cell acute lymphoblastic leukemia (T-ALL) and T-cell lymphoblastic lymphoma (T-LBL) in adult and pediatric patients age 1 year and older whose disease has not responded to or has relapsed following treatment with at least two chemotherapy regimens. (1)

2 DOSAGE AND ADMINISTRATION

- Adult Dose: 1,500 mg/m^2 administered by intravenous infusion over 2 hours on Days 1, 3, and 5 repeated every 21 days. (2.1)
- Pediatric Dose: 650 mg/m^2 administered by intravenous infusion over 1 hour daily for 5 consecutive days repeated every 21 days. (2.1)
- Discontinue treatment for neurologic reactions greater than or equal to Grade 2. (2.2)
- Dosage may be delayed for hematologic reactions. (2.2)
- Take measures to prevent hyperuricemia. (2.4)

3 DOSAGE FORMS AND STRENGTHS

Injection: 250 mg/50 mL (5 mg/mL) single-dose vial. (3)

4 CONTRAINDICATIONS

None.

5 WARNINGS AND PRECAUTIONS

- Neurologic Adverse Reactions: Severe neurologic reactions have been reported. Monitor for signs and symptoms of neurologic toxicity. (5.1)
- Hematologic Reactions: Complete blood counts including platelets should be monitored regularly. (5.2)
- Embryo-Fetal Toxicity: Can cause fetal harm. Advise females of reproductive potential of the potential risk to the fetus and to use effective contraception; and advise males to use condoms. (5.3, 8.1, 8.3)
- Effects on Ability to Drive and Use Machines: Somnolence may occur. Advise patients to refrain from these activities until somnolence has resolved. (5.6)

6 ADVERSE REACTIONS

The most common (≥ 20%) adverse reactions were:

- Adult: anemia, thrombocytopenia, neutropenia, nausea, diarrhea, vomiting, constipation, fatigue, pyrexia, cough, and dyspnea. (6.1)
- Pediatric: anemia, neutropenia, thrombocytopenia, and leukopenia. (6.1)

The most common (> 10%) neurological adverse reactions were:

- Adult: somnolence, dizziness, peripheral neurologic disorders, hypoesthesia, headache, and paresthesia. (6.1)
- Pediatric: headache and peripheral neurologic disorders. (6.1)

To report SUSPECTED ADVERSE REACTIONS, contact Novartis Pharmaceuticals Corporation at 1-888-669-6682 or FDA at 1-800-FDA-1088 or www.fda.gov/medwatch.

7 DRUG INTERACTIONS

Administration in combination with adenosine deaminase (ADA) inhibitors, such as pentostatin, is not recommended. (7, 12.3)

8 USE IN SPECIFIC POPULATIONS

- Lactation: Advise not to breastfeed. (8.2)
- Renal Impairment: Closely monitor patients with moderate or severe renal impairment for toxicities. (8.6)
- Hepatic Impairment: Closely monitor patients with severe hepatic impairment for toxicities. (8.7)

FULL PRESCRIBING INFORMATION

WARNING: NEUROLOGIC ADVERSE REACTIONS

Severe neurologic adverse reactions have been reported with the use of ARRANON®. These adverse reactions have included altered mental states including severe somnolence, central nervous system effects including convulsions, and peripheral neuropathy ranging from numbness and paresthesias to motor weakness and paralysis. There have also been reports of adverse reactions associated with demyelination, and ascending peripheral neuropathies similar in appearance to Guillain-Barré syndrome [see Warnings and Precautions (5.1)].

Full recovery from these adverse reactions has not always occurred with cessation of therapy with ARRANON. Monitor frequently for signs and symptoms of neurologic toxicity during treatment with ARRANON. Discontinue ARRANON for neurologic adverse reactions of NCI Common Toxicity Criteria for Adverse Events (CTCAE) Grade 2 or greater [see Warnings and Precautions (5.1)].

1 INDICATIONS AND USAGE

ARRANON is indicated for the treatment of T-cell acute lymphoblastic leukemia (T-ALL) and T-cell lymphoblastic lymphoma (T-LBL) in adult and pediatric patients age 1 year and older whose disease has not responded to or has relapsed following treatment with at least 2 chemotherapy regimens.

2 DOSAGE AND ADMINISTRATION

2.1 Recommended Dosage

This product is for intravenous use only.

Adult Dosage: The recommended adult dose of ARRANON is 1,500 mg/m^2 administered by intravenous infusion over 2 hours on Days 1, 3, and 5 repeated every 21 days. Administer ARRANON undiluted.

Pediatric Dosage: The recommended pediatric dose of ARRANON is 650 mg/m^2 administered by intravenous infusion over 1 hour daily for 5 consecutive days repeated every 21 days. Administer ARRANON undiluted.

The recommended duration of treatment for adult and pediatric patients has not been clearly established. In clinical trials, treatment was generally continued until there was evidence of disease progression, the patient experienced unacceptable toxicity, the patient became a candidate for hematopoietic stem cell transplantation (HSCT), or the patient no longer continued to benefit from treatment.

2.2 Dosage Modification

Discontinue ARRANON if the patient develops a neurologic adverse reaction of NCI CTCAE Grade 2 or greater. Dosage may be delayed for other toxicity, including hematologic toxicity [see Boxed Warning, Warnings and Precautions (5.1, 5.2)].

2.3 Dosage in Special Populations

ARRANON has not been studied in patients with renal or hepatic dysfunction [see Use in Specific Populations (8.6, 8.7)]. No dose adjustment is recommended for patients with a creatinine clearance (CLCr) greater than or equal to 50 mL/min [see Clinical Pharmacology (12.3)]. There are insufficient data to support a dose recommendation for patients with a CLCr less than 50 mL/min.

2.4 Prevention of Hyperuricemia

Take precautions against hyperuricemia (e.g., hydration, urine alkalinization, and prophylaxis with allopurinol) [see Warnings and Precautions (5.4)].

2.5 Instructions for Handling, Preparation, and Administration

Handling: ARRANON is a hazardous drug. Caution should be used during handling and preparation. Use of gloves and other protective clothing to prevent skin contact is recommended. Proper aseptic technique should be used. Guidelines for proper handling and disposal of anticancer drugs have been published.^1

Preparation and Administration: Administer ARRANON undiluted. Transfer the appropriate dose of ARRANON into polyvinylchloride (PVC) infusion bags or glass containers and administer as a 2-hour infusion in adult patients and as a 1-hour infusion in pediatric patients.

Prior to administration, inspect the drug product visually for particulate matter and discoloration.

Stability: ARRANON Injection is stable in PVC infusion bags and glass containers for up to 8 hours at up to 30ºC.

3 DOSAGE FORMS AND STRENGTHS

ARRANON Injection 250 mg/50 mL (5 mg/mL) is supplied as a clear, colorless, sterile solution in Type I, clear glass single-dose vials with a gray bromobutyl rubber stopper (not made with natural rubber latex) and an aluminum seal with a snap-off cap.

4 CONTRAINDICATIONS

None.

5 WARNINGS AND PRECAUTIONS

5.1 Neurologic Adverse Reactions

Nervous system adverse reactions of any grade were reported for 223 (76%) adult patients across the Phase I and Phase II trials, and Grade 3 or higher (severe, life-threatening, or fatal) adverse reactions were reported for 55 (19%) patients following initiation of ARRANON therapy [see Adverse Reactions (6.1)]. Based on patients with complete data, the median time to onset of first event is 5 days from start of first infusion (range: 1-166), and the median duration is 6 days (range: 1-393 days).

Nervous system adverse reactions of any grade were reported for 69 (42%) pediatric patients across the Phase I and Phase II trials, and Grade 3 or higher (severe, life-threatening, or fatal) adverse reactions were reported for 25 (15%) patients following initiation of ARRANON therapy [see Adverse Reactions (6.1)]. Based on patients with complete data, the median time to onset of first event is 8 days from start of first infusion (range: 1-269), and the median duration is 2 days (range: 1-82 days).

Common signs and symptoms of ARRANON-related neurotoxicity include somnolence, headache, paresthesia and dysesthesia, dizziness, neuropathy (sensory and motor), cerebellar disturbances and tremor. Severe neurologic toxicity can manifest as coma, status epilepticus, craniospinal demyelination, or ascending neuropathy similar in presentation to Guillain-Barré syndrome.

Full recovery from these adverse reactions has not always occurred with cessation of therapy with ARRANON. Patients treated previously or concurrently with intrathecal chemotherapy or previously with craniospinal irradiation may be at increased risk for neurologic adverse events.

Monitor patients frequently for signs and symptoms of neurologic toxicity during and for at least 24 hours after completion of treatment with ARRANON. Discontinue ARRANON for neurologic adverse reactions of NCI CTCAE Grade 2 or greater and provide supportive care [see Dosage and Administration (2.2), Adverse Reactions (6.1)].

5.2 Hematologic Adverse Reactions

Leukopenia, thrombocytopenia, anemia, and neutropenia, including febrile neutropenia, have been associated with ARRANON therapy. Complete blood counts including platelets should be monitored regularly [see Dosage and Administration (2.2), Adverse Reactions (6.1)].

5.3 Embryo-Fetal Toxicity

Based on its mechanism of action and findings in animal studies, ARRANON can cause fetal harm when administered to a pregnant woman [see Clinical Pharmacology (12.1)]. In animal reproduction studies, intravenous administration of nelarabine to pregnant rabbits during the period of organogenesis resulted in teratogenicity at maternal doses below the recommended human adult dose of 1,500 mg/m^2/day (see Data).
Advise pregnant women of the potential risk to the fetus. Advise females of reproductive potential to use effective contraception during treatment with ARRANON. Advise males with female partners of reproductive potential to use condoms during treatment with ARRANON and for 3 months after the last dose [see Use in Specific Populations (8.1, 8.3), Nonclinical Toxicology (13.1)].

5.4 Tumor Lysis Syndrome

Patients receiving ARRANON should receive intravenous hydration according to standard medical practice for the management of hyperuricemia in patients at risk for tumor lysis syndrome. Consideration should be given to the use of allopurinol in patients at risk of hyperuricemia [see Dosage and Administration (2.4)].

5.5 Vaccinations

Avoid the administration of live vaccines to immunocompromised patients.

5.6 Effects on Ability to Drive and Use Machines

Patients treated with ARRANON may experience somnolence during and for several days after treatment [see Adverse Reactions (6.1)]. Advise patients to refrain from driving or engaging in hazardous occupations or activities until somnolence has resolved.

6 ADVERSE REACTIONS

The following clinically-significant adverse reactions are discussed in greater detail in other sections of the label:

- Neurologic [see Boxed Warning, Warnings and Precautions (5.1)]
- Hematologic [see Warnings and Precautions (5.2)]
- Tumor Lysis Syndrome [see Warnings and Precautions (5.4)]
- Effects on Ability to Drive and Use Machines [see Warnings and Precautions (5.6)]

6.1 Clinical Trials Experience

Because clinical trials are conducted under widely varying conditions, adverse reaction rates observed in the clinical trials of a drug cannot be directly compared with rates in the clinical trials of another drug and may not reflect the rates observed in practice.

Relapsed or Refractory T-ALL and T-LBL

ARRANON was studied in 459 patients in Phase I and Phase II clinical trials.

Adult Patient: The safety profile of ARRANON is based on data from 103 adult patients treated with the recommended dose and schedule in 2 studies: an adult T-ALL/T-cell T-LBL trial and an adult chronic lymphocytic leukemia trial.

The most common adverse reactions in adults were fatigue; gastrointestinal disorders (nausea, diarrhea, vomiting, and constipation); hematologic disorders (anemia, neutropenia, and thrombocytopenia); respiratory disorders (cough and dyspnea); nervous system disorders (somnolence and dizziness); and pyrexia.

The most common adverse reactions in adults by Body System, including severe or life-threatening adverse reactions (NCI CTCAE Grade 3 or Grade 4) and fatal adverse reactions (Grade 5) are shown in Table 1.

Table 1. Most Commonly Reported (≥ 5% Overall) Adverse Reactions in Adult Patients Treated With 1,500 mg/m^2 of ARRANON Administered by Intravenous Infusion Over 2 Hours on Days 1, 3, and 5 Repeated Every 21 Days
 | Percentage of Patients (N = 103)
 | Toxicity Grade
Body System | Grade 3 | Grades 4 and 5a | All Grades
Adverse Reaction | % | % | %
Blood and Lymphatic System Disorders
Anemia | 20 | 14 | 99
Thrombocytopenia | 37 | 22 | 86
Neutropenia | 14 | 49 | 81
Febrile neutropenia | 9 | 1 | 12
Cardiac Disorders
Sinus tachycardia | 1 | 0 | 8
Gastrointestinal Disorders
Nausea | 0 | 0 | 41
Diarrhea | 1 | 0 | 22
Vomiting | 1 | 0 | 22
Constipation | 1 | 0 | 21
Abdominal pain | 1 | 0 | 9
Stomatitis | 1 | 0 | 8
Abdominal distension | 0 | 0 | 6
General Disorders and Administration Site Conditions
Fatigue | 10 | 2 | 50
Pyrexia | 5 | 0 | 23
Asthenia | 0 | 1 | 17
Edema, peripheral | 0 | 0 | 15
Edema | 0 | 0 | 11
Pain | 3 | 0 | 11
Rigors | 0 | 0 | 8
Gait, abnormal | 0 | 0 | 6
Chest pain | 0 | 0 | 5
Noncardiac chest pain | 0 | 1 | 5
Infections
Infection | 2 | 1 | 9
Pneumonia | 4 | 1 | 8
Sinusitis | 1 | 0 | 7
Hepatobiliary Disorders
AST increased | 1 | 1 | 6
Metabolism and Nutrition Disorders
Anorexia | 0 | 0 | 9
Dehydration | 3 | 1 | 7
Hyperglycemia | 1 | 0 | 6
Musculoskeletal and Connective Tissue Disorders
Myalgia | 1 | 0 | 13
Arthralgia | 1 | 0 | 9
Back pain | 0 | 0 | 8
Muscular weakness | 5 | 0 | 8
Pain in extremity | 1 | 0 | 7
Nervous System Disorders (see Table 2)
Psychiatric Disorders
Confusional state | 2 | 0 | 8
Insomnia | 0 | 0 | 7
Depression | 1 | 0 | 6
Respiratory, Thoracic, and Mediastinal Disorders
Cough | 0 | 0 | 25
Dyspnea | 4 | 2 | 20
Pleural effusion | 5 | 1 | 10
Epistaxis | 0 | 0 | 8
Dyspnea, exertional | 0 | 0 | 7
Wheezing | 0 | 0 | 5
Vascular Disorders
Petechiae | 2 | 0 | 12
Hypotension | 1 | 1 | 8

Abbreviation: AST, aspartate transaminase.
  a Five (5) patients had a fatal adverse reaction. Fatal adverse reactions included hypotension (n = 1), respiratory arrest (n = 1), pleural effusion/pneumothorax (n = 1), pneumonia (n = 1), and cerebral hemorrhage/coma/leukoencephalopathy (n = 1).

Other Adverse Reactions: Blurred vision was also reported in 4% of adult patients.

There was a single report of biopsy-confirmed progressive multifocal leukoencephalopathy in the adult patient population.

Neurologic Adverse Reactions: Nervous system adverse reactions, were reported for 76% of adult patients across the Phase I and Phase II trials. The most common neurologic adverse reactions (≥ 2%) in adult patients including all grades (NCI CTCAE) are shown in Table 2.

Table 2. Neurologic Adverse Reactions (≥ 2%) in Adult Patients Treated With 1,500 mg/m^2 of ARRANON Administered by Intravenous Infusion Over 2 Hours on Days 1, 3, and 5 Repeated Every 21 Days
 | Percentage of Patients (N =103)
Nervous System Disorders | Grade 1 | Grade 2 | Grade 3 | Grade 4 | All Grades
Adverse Reaction | % | % | % | % | %
Somnolence | 20 | 3 | 0 | 0 | 23
Dizziness | 14 | 8 | 0 | 0 | 21
Peripheral neurologic disorders, any adverse reaction | 8 | 12 | 2 | 0 | 21
Neuropathy | 0 | 4 | 0 | 0 | 4
Peripheral neuropathy | 2 | 2 | 1 | 0 | 5
Peripheral motor neuropathy | 3 | 3 | 1 | 0 | 7
Peripheral sensory neuropathy | 7 | 6 | 0 | 0 | 13
Hypoesthesia | 5 | 10 | 2 | 0 | 17
Headache | 11 | 3 | 1 | 0 | 15
Paresthesia | 11 | 4 | 0 | 0 | 15
Ataxia | 1 | 6 | 2 | 0 | 9
Depressed level of consciousness | 4 | 1 | 0 | 1 | 6
Tremor | 2 | 3 | 0 | 0 | 5
Amnesia | 2 | 1 | 0 | 0 | 3
Dysgeusia | 2 | 1 | 0 | 0 | 3
Balance disorder | 1 | 1 | 0 | 0 | 2
Sensory loss | 0 | 2 | 0 | 0 | 2

One patient had a fatal neurologic adverse reaction, cerebral hemorrhage/coma/leukoencephalopathy.

Most nervous system adverse reactions in the adult patients were evaluated as Grade 1 or 2. The additional Grade 3 adverse reactions in adult patients, were aphasia, convulsion, hemiparesis, and loss of consciousness, each reported in 1 patient (1%). The additional Grade 4 adverse reactions were cerebral hemorrhage, coma, intracranial hemorrhage, leukoencephalopathy, and metabolic encephalopathy, each reported in one patient (1%).

The other neurologic adverse reactions reported as Grade 1, 2, or unknown in adult patients were abnormal coordination, burning sensation, disturbance in attention, dysarthria, hyporeflexia, neuropathic pain, nystagmus, peroneal nerve palsy, sciatica, sensory disturbance, sinus headache, and speech disorder, each reported in one patient (1%).

Pediatric Patient: The safety profile for children is based on data from 84 pediatric patients treated with the recommended dose and schedule in a T-ALL/T-LBL treatment trial.

The most common adverse reactions in pediatric patients were hematologic disorders (anemia, leukopenia, neutropenia, and thrombocytopenia). Of the non-hematologic adverse reactions in pediatric patients, the most frequent adverse reactions reported were headache, increased transaminase levels, decreased blood potassium, decreased blood albumin, increased blood bilirubin, and vomiting.

The most common adverse reactions in pediatric patients by System Organ Class including severe or life threatening adverse reactions (NCI CTCAE Grade 3 or Grade 4) and fatal adverse reactions (Grade 5) are shown in Table 3.

Table 3. Most Commonly Reported (≥ 5% Overall) Adverse Reactions in Pediatric Patients Treated With 650 mg/m^2 of ARRANON Administered by Intravenous Infusion Over 1 Hour Daily for 5 Consecutive Days Repeated Every 21 Days
 | Percentage of Patients (N = 84)
 | Toxicity Grade
Body System | Grade 3 | Grade 4 and 5a | All Grades
Adverse Reaction | % | % | %
Blood and Lymphatic System Disorders
Anemia | 45 | 10 | 95
Neutropenia | 17 | 62 | 94
Thrombocytopenia | 27 | 32 | 88
Leukopenia | 14 | 7 | 38
Hepatobiliary Disorders
Transaminases increased | 4 | 0 | 12
Blood albumin decreased | 5 | 1 | 10
Blood bilirubin increased | 7 | 2 | 10
Metabolic/Laboratory
Blood potassium decreased | 4 | 2 | 11
Blood calcium decreased | 1 | 1 | 8
Blood creatinine increased | 0 | 0 | 6
Blood glucose decreased | 4 | 0 | 6
Blood magnesium decreased | 2 | 0 | 6
Nervous System Disorders (see Table 4)
Gastrointestinal Disorders
Vomiting | 0 | 0 | 10
General Disorders & Administration Site Conditions
Asthenia | 1 | 0 | 6
Infections & Infestations
Infection | 2 | 1 | 5

a Three (3) patients had a fatal adverse reaction. Fatal adverse reactions included neutropenia and pyrexia (n = 1), status epilepticus/seizure (n = 1), and fungal pneumonia (n = 1).

Neurologic Adverse Reactions: Nervous system adverse reactions were reported for 42% of pediatric patients across the Phase I and Phase II trials. The most common neurologic adverse reactions (≥ 2%) in pediatric patients including all grades (NCI CTCAE) are shown in Table 4.

Table 4. Neurologic Adverse Reactions (≥ 2%) in Pediatric Patients Treated With 650 mg/m^2 of ARRANON Administered by Intravenous Infusion Over 1 Hour Daily for 5 Consecutive Days Repeated Every 21 Days
 | Percentage of Patients (N = 84)
Nervous System Disorders | Grade 1 | Grade 2 | Grade 3 | Grade 4 and 5a | All Grades
Adverse Reaction | % | % | % | % | %
Headache | 8 | 2 | 4 | 2 | 17
Peripheral neurologic disorders, any adverse reaction | 1 | 4 | 7 | 0 | 12
Peripheral neuropathy | 0 | 4 | 2 | 0 | 6
Peripheral motor neuropathy | 1 | 0 | 2 | 0 | 4
Peripheral sensory neuropathy | 0 | 0 | 6 | 0 | 6
Somnolence | 1 | 4 | 1 | 1 | 7
Hypoesthesia | 1 | 1 | 4 | 0 | 6
Seizures | 0 | 0 | 0 | 6 | 6
Convulsions | 0 | 0 | 0 | 3 | 4
Grand mal convulsions | 0 | 0 | 0 | 1 | 1
Status epilepticus | 0 | 0 | 0 | 1 | 1
Motor dysfunction | 1 | 1 | 1 | 0 | 4
Nervous system disorder | 1 | 2 | 0 | 0 | 4
Paresthesia | 0 | 2 | 1 | 0 | 4
Tremor | 1 | 2 | 0 | 0 | 4
Ataxia | 1 | 0 | 1 | 0 | 2

a One (1) patient had a fatal neurologic adverse reaction, status epilepticus.

The other Grade 3 neurologic adverse reaction in pediatric patients was hypertonia reported in 1 patient (1%). The additional Grade 4 neurologic adverse reactions, were third nerve paralysis, and sixth nerve paralysis, each reported in 1 patient (1%).

The other neurologic adverse reactions reported as Grade 1, 2, or unknown in pediatric patients were dysarthria, encephalopathy, hydrocephalus, hyporeflexia, lethargy, mental impairment, paralysis, and sensory loss, each reported in 1 patient (1%).

ARRANON in Combination with Multi-Agent Chemotherapy in T-ALL and T-LBL

ARRANON was studied in combination with multi-agent chemotherapy in a randomized clinical trial [NCT00408005]. The safety population in this trial included 804 patients with newly-diagnosed T-ALL (85%) or T-LBL (15%) treated with (n = 411) or without (n =393) ARRANON in combination with the augmented Berlin-Frankfurt-Münster chemotherapy regimen (aBFM) after initial induction therapy. Patients assigned to ARRANON received 650 mg/m^2 intravenously over 1 hour daily for 5 consecutive days, during consolidation Days 1 to 5 and 43 to 47, delayed intensification Days 29 to 33, and during the initial 3 courses of maintenance Days 29 to 33. The median age on enrollment was 9.5 years (range: 1-29), the majority of patients were male (73%) and white (69%). Sixty-five percent of patients assigned to the ARRANON arms received at least 85% of the planned dose through the third course of maintenance therapy compared to 79% of patients on the control arms who received 3 courses of maintenance therapy.

There was one fatal neurological adverse reaction in the ARRANON arm. The incidence of the following Grades 3 and 4 adverse reactions were higher in the ARRANON treated arms compared to the control arms: abnormal transaminases, motor and sensory neuropathy, nausea and vomiting, and dehydration. The incidence of seizures of any grade was 3% (14 of 411). Rhabdomyolysis was diagnosed in 2% (7 of 411) of ARRANON treated patients and occurred after the first course of ARRANON during the consolidation phase of therapy.

6.2 Postmarketing Experience

The following adverse reactions have been identified during post-approval use of ARRANON. Because these reactions are reported voluntarily from a population of uncertain size, it is not always possible to reliably estimate their frequency or establish a causal relationship to drug exposure.

Infections and Infestations: Fatal opportunistic infections

Metabolism and Nutrition Disorders: Tumor lysis syndrome

Nervous System Disorders: Demyelination and ascending peripheral neuropathies similar in appearance to Guillain-Barré syndrome

Musculoskeletal and Connective Disorders: Rhabdomyolysis, blood creatine phosphokinase increased

7 DRUG INTERACTIONS

Administration of ARRANON in combination with adenosine deaminase (ADA) inhibitors, such as pentostatin, is not recommended [see Clinical Pharmacology (12.3)].

8 USE IN SPECIFIC POPULATIONS

8.1 Pregnancy

Risk Summary

Based on its mechanism of action and findings in animal studies, ARRANON can cause fetal harm when administered to a pregnant woman [see Clinical Pharmacology (12.1)]. Limited available data with ARRANON use in pregnant women are insufficient to determine a drug-associated risk for major birth defects, miscarriage or adverse maternal, or fetal outcomes. There are risks to the pregnant woman associated with untreated leukemia or lymphoma (see Clinical Considerations). In animal reproduction studies, intravenous administration of nelarabine to pregnant rabbits during the period of organogenesis resulted in teratogenicity at maternal doses below the recommended human adult dose of 1,500 mg/m^2/day (see Data). Advise pregnant women of the potential risk to the fetus.

The estimated background risk of major birth defects and miscarriage for the indicated population is unknown. All pregnancies have a background risk of birth defect, loss, or other adverse outcomes. In the U.S. general population, the estimated background risk of major birth defects and miscarriage in clinically recognized pregnancies are 2% to 4% and 15% to 20%, respectively.

Clinical Considerations

Disease-Associated Maternal and/or Embryo-fetal Risk

There are risks to the mother from untreated leukemia or lymphoma, including anemia, thrombocytopenia, and death.

Data

Animal Data

In an embryo-fetal development study in which pregnant rabbits were administered daily doses of nelarabine during organogenesis, increased incidences of fetal malformations, anomalies, and variations were observed at doses greater than or equal to 360 mg/m^2/day (8-hour IV infusion; approximately 25% of the recommended human adult dose compared on a mg/m^2 basis), which was the lowest dose tested. Cleft palate was seen in rabbits given 3600 mg/m^2/day (approximately 2-fold the adult dose), absent pollices (digits) in rabbits given greater than or equal to 1200 mg/m^2/day (approximately 75% of the recommended adult dose), while absent gall bladder, absent accessory lung lobes, fused or extra sternebrae, and delayed ossification was seen at all doses. Maternal body weight gain and fetal body weights were reduced in rabbits given 3600 mg/m^2/day (approximately 2-fold the adult dose), but could not account for the increased incidence of malformations seen at this or lower administered doses.

8.2 Lactation

Risk Summary

There are no data on the presence of nelarabine or ara-G in human or animal milk, the effect on the breastfed child, or the effect on milk production. Because of the potential for serious adverse reactions in the breastfed child from ARRANON, such as severe neurological reactions, advise women not to breastfeed during treatment with ARRANON.

8.3 Females and Males of Reproductive Potential

Pregnancy Testing

ARRANON can cause fetal harm when administered to a pregnant woman [see Use in Specific Populations (8.1)]. Verify the pregnancy status of females of reproductive potential prior to starting treatment with ARRANON.

Contraception

Females

ARRANON can cause fetal harm when administered to a pregnant woman [see Warnings and Precautions (5.3), Use in Specific Populations (8.1)]. Because of the potential for genotoxicity, advise females of reproductive potential to use effective contraception during treatment with ARRANON.

Males

Because of the potential for genotoxicity, advise males (including those who have had vasectomies) with female partners of reproductive potential to use condoms during treatment with ARRANON and for 3 months after the last dose [see Nonclinical Toxicology (13.1)].

8.4 Pediatric Use

The safety and effectiveness of ARRANON for relapsed or refractory T-ALL and T-LBL has been established in pediatric patients age 1 year and older. The effectiveness of ARRANON in pediatric patients is supported by one single-arm clinical trial, and safety has been asssessed in 165 pediatric patients age 1 year and older across multiple Phase I and Phase II trials. The trial establishing efficacy included 84 patients age 21 years and younger, who had relapsed or refractory T-ALL or T-LBL. The most frequent adverse reactions of any grade occurring on treatment in this study were hematologic laboratory abnormalities. Hematologic toxicity observed in the pediatric population was higher than that seen in the adult population [see Dosage and Administration (2.1), Adverse Reactions (6.1), Clinical Studies (14.2)].

Nervous system adverse reactions have been reported for 42% of pediatric patients across the Phase I and Phase II trials. The incidence of nervous system adverse reactions was less in the pediatric population than that seen in adult patients with relapsed/refractory T-ALL/T-LBL [see Adverse Reactions (6.1)].

In a phase III study of ARRANON in combination with multi-agent chemotherapy as first-line therapy, there were 411 patients with T-ALL or T-LBL treated with ARRANON. The safety profile in the 357 patients age 1 to 16 years was consistent with that seen in older patients in the study [see Adverse Reactions (6.1)].

Due to lack of long-term follow up data, a determination of the impact of ARRANON on the growth and pubertal development of pediatric patients cannot be made.

8.5 Geriatric Use

Clinical studies of ARRANON did not include sufficient numbers of patients age 65 and over to determine whether they respond differently from younger patients. In an exploratory analysis, increasing age, especially age 65 years and older, appeared to be associated with increased rates of neurologic adverse reactions. Because elderly patients are more likely to have decreased renal function, care should be taken in dose selection [see Use in Specific Populations (8.6)].

8.6 Renal Impairment

Ara-G clearance decreased as renal function decreased [see Clinical Pharmacology (12.3)]. Because the risk of adverse reactions to this drug may be greater in patients with moderate (CLCr 30 to 50 mL/min) or severe (CLCr less than 30 mL/min) renal impairment, these patients should be closely monitored for toxicities when treated with ARRANON [see Dosage and Administration (2.3)].

8.7 Hepatic Impairment

The influence of hepatic impairment on the pharmacokinetics of nelarabine has not been evaluated. Because the risk of adverse reactions to this drug may be greater in patients with severe hepatic impairment (total bilirubin greater than 3 times upper limit of normal), these patients should be closely monitored for toxicities when treated with ARRANON.

10 OVERDOSAGE

There is no known antidote for overdoses of ARRANON. It is anticipated that overdosage would result in severe neurotoxicity (possibly including paralysis, coma), myelosuppression, and potentially death. In the event of overdose, supportive care consistent with good clinical practice should be provided.

At a dose of 2200 mg/m^2 given on Days 1, 3, and 5 every 21 days, 2 patients developed a significant Grade 3 ascending sensory neuropathy. Magnetic resonance imaging evaluations of the 2 patients demonstrated findings consistent with a demyelinating process in the cervical spine.

11 DESCRIPTION

ARRANON (nelarabine) is a prodrug of the cytotoxic deoxyguanosine analogue, 9-β-D-arabinofuranosylguanine (ara-G).

The chemical name for nelarabine is 2-amino-9-β-D-arabinofuranosyl-6-methoxy-9H-purine. It has the molecular formula C11H15N5O5 and a molecular weight of 297.27. Nelarabine has the following structural formula:

Nelarabine is slightly soluble to soluble in water and melts with decomposition between 209ºC and 217ºC.

ARRANON (nelarabine) injection is supplied as a clear, colorless, sterile solution in glass single-dose vials. Each vial contains 250 mg of nelarabine (5 mg nelarabine per mL) and the inactive ingredient sodium chloride (4.5 mg per mL) in Water for Injection, USP. ARRANON is intended for intravenous infusion.

Hydrochloric acid and sodium hydroxide may have been used to adjust the pH. The solution pH ranges from 5.0 to 7.0.

12 CLINICAL PHARMACOLOGY

12.1 Mechanism of Action

Nelarabine is a prodrug of the deoxyguanosine analogue 9-β-D-arabinofuranosylguanine (ara-G), a nucleoside metabolic inhibitor. Nelarabine is demethylated by ADA to ara-G, mono-phosphorylated by deoxyguanosine kinase and deoxycytidine kinase, and subsequently converted to the active 5’-triphosphate, ara-GTP. Accumulation of ara-GTP in leukemic blasts allows for incorporation into deoxyribonucleic acid (DNA), leading to inhibition of DNA synthesis and cell death. Other mechanisms may contribute to the cytotoxic and systemic toxicity of nelarabine.

12.3 Pharmacokinetics

Absorption: Following intravenous administration of nelarabine to adult patients with refractory leukemia or lymphoma, plasma ara-G Cmax values generally occurred at the end of the nelarabine infusion and were generally higher than nelarabine Cmax values, suggesting rapid and extensive conversion of nelarabine to ara-G. Mean plasma nelarabine and ara-G Cmax values were 5.0 ± 3.0 mcg/mL and 31.4 ± 5.6 mcg/mL, respectively, after a 1,500 mg/m^2 nelarabine dose infused over 2 hours in adult patients. The area under the concentration-time curve (AUC) of ara-G is 37 times higher than that for nelarabine on Day 1 after nelarabine IV infusion of 1,500 mg/m^2 dose (162 ± 49 mcg.h/mL versus 4.4 ± 2.2 mcg.h/mL, respectively). Comparable Cmax and AUC values were obtained for nelarabine between Days 1 and 5 at the nelarabine adult dosage of 1,500 mg/m^2, indicating that nelarabine does not accumulate after multiple-dosing. There are not enough ara-G data to make a comparison between Day 1 and Day 5. After a nelarabine adult dose of 1,500 mg/m^2, intracellular Cmax for ara-GTP appeared within 3 to 25 hours on Day 1. Exposure (AUC) to intracellular ara-GTP was 532 times higher than that for nelarabine and 14 times higher than that for ara-G (2,339 ± 2,628 mcg.h/mL versus 4.4 ± 2.2 mcg.h/mL and 162 ± 49 mcg.h/mL, respectively). Because the intracellular levels of ara-GTP were so prolonged, its elimination half-life could not be accurately estimated.

Distribution: Nelarabine and ara-G are extensively distributed throughout the body. For nelarabine, VSS values were 197 ± 216 L/m^2 in adult patients. For ara-G, VSS/F values were 50 ± 24 L/m^2 in adult patients.

Nelarabine and ara-G are not substantially bound to human plasma proteins (< 25%) in vitro, and binding is independent of nelarabine or ara-G concentrations up to 600 μM.

Metabolism: The principal route of metabolism for nelarabine is O-demethylation by ADA to form ara-G, which undergoes hydrolysis to form guanine. In addition, some nelarabine is hydrolyzed to form methylguanine, which is O-demethylated to form guanine. Guanine is N-deaminated to form xanthine, which is further oxidized to yield uric acid.

Excretion: Nelarabine and ara-G are partially eliminated by the kidneys. Mean urinary excretion of nelarabine and ara-G was 6.6 ± 4.7% and 27 ± 15% of the administered dose, respectively, in 28 adult patients over the 24 hours after nelarabine infusion on Day 1. Renal clearance averaged 24 ± 23 L/h for nelarabine and 6.2 ± 5.0 L/h for ara-G in 21 adult patients. Combined Phase I pharmacokinetic data at nelarabine doses of 199 to 2900 mg/m^2 (n = 66 adult patients) indicate that the mean clearance (CL) of nelarabine is 197 ± 189 L/h/m^2 on Day 1. The apparent clearance of ara-G (CL/F) is 10.5 ± 4.5 L/h/m^2 on Day 1. Nelarabine and ara-G are rapidly eliminated from plasma with a mean half-life of 18 minutes and 3.2 hours, respectively, in adult patients.

Pediatrics: No pharmacokinetic data are available in pediatric patients at the once-daily 650 mg/m^2 nelarabine dosage. Combined Phase I pharmacokinetic data at nelarabine doses of 104 to 2900 mg/m^2 indicate that the mean clearance (CL) of nelarabine is about 30% higher in pediatric patients than in adult patients (259 ± 409 L/h/m^2 versus 197 ± 189 L/h/m^2, respectively) (n = 66 adults, n = 22 pediatric patients) on Day 1. The apparent clearance of ara-G (CL/F) is comparable between the 2 groups (10.5 ± 4.5 L/h/m^2 in adult patients and 11.3 ± 4.2 L/h/m^2 in pediatric patients) on Day 1. Nelarabine and ara-G are extensively distributed throughout the body. For nelarabine, VSS values were 213 ± 358 L/m^2 in pediatric patients. For ara-G, VSS/F values were 33 ± 9.3 L/m^2 in pediatric patients. Nelarabine and ara-G are rapidly eliminated from plasma in pediatric patients, with a half-life of 13 minutes and 2 hours, respectively.

Effect of Age: Age has no effect on the pharmacokinetics of nelarabine or ara-G in adults. Decreased renal function, which is more common in the elderly, may reduce ara-G clearance [see Use in Specific Populations (8.5)].

Effect of Gender: Gender has no effect on nelarabine or ara-G pharmacokinetics.

Effect of Race: In general, nelarabine mean clearance and volume of distribution values tend to be higher in whites (n = 63) than in blacks (by about 10%) (n = 15). The opposite is true for ara-G; mean apparent clearance and volume of distribution values tend to be lower in whites than in blacks (by about 15% to 20%). No differences in safety or effectiveness were observed between these groups.

Effect of Renal Impairment: The pharmacokinetics of nelarabine and ara-G have not been specifically studied in renally impaired or hemodialyzed patients. Nelarabine is excreted by the kidney to a small extent (5% to 10% of the administered dose). Ara-G is excreted by the kidney to a greater extent (20% to 30% of the administered nelarabine dose). In the combined Phase I trials, patients were categorized into 3 groups: normal with CLCr greater than 80 mL/min (n = 67), mild with CLCr = 50 to 80 mL/min (n = 15), and moderate with CLCr less than 50 mL/min (n = 3). The mean apparent clearance (CL/F) of ara-G was about 15% and 40% lower in patients with mild and moderate renal impairment, respectively, than in patients with normal renal function [see Use in Specific Populations (8.6), Dosage and Administration (2.3)]. No differences in safety or effectiveness were observed.

Effect of Hepatic Impairment: The influence of hepatic impairment on the pharmacokinetics of nelarabine has not been evaluated [see Use in Specific Populations (8.7)].

Drug Interactions: Cytochrome P450: Nelarabine and ara-G did not significantly inhibit the activities of the human hepatic cytochrome P450 isoenzymes 1A2, 2A6, 2B6, 2C8, 2C9, 2C19, 2D6, or 3A4 in vitro at concentrations of nelarabine and ara-G up to 100 μM.

Fludarabine: Administration of fludarabine 30 mg/m^2 as a 30-minute infusion 4 hours before a 1200-mg/m^2 infusion of nelarabine did not affect the pharmacokinetics of nelarabine, ara-G, or ara-GTP in 12 patients with refractory leukemia.

Pentostatin: There is in vitro evidence that pentostatin is a strong inhibitor of ADA. Inhibition of ADA may result in a reduction in the conversion of the prodrug nelarabine to its active moiety and consequently in a reduction in efficacy of nelarabine and/or change in adverse reaction profile of either drug [see Drug Interactions (7)].

13 NONCLINICAL TOXICOLOGY

13.1 Carcinogenesis, Mutagenesis, Impairment of Fertility

Carcinogenicity testing of nelarabine has not been done. However, nelarabine was mutagenic when tested in vitro in L5178Y/TK mouse lymphoma cells with and without metabolic activation. No studies have been conducted in animals to assess genotoxic potential or effects on fertility. The effect on human fertility is unknown.

14 CLINICAL STUDIES

14.1 Adult Clinical Trial in Relapsed or Refractory T-ALL and T-LBL

The safety and efficacy of ARRANON in adult patients were studied in a clinical trial which included 39 treated patients, 28 who had T-ALL or T-LBL that had relapsed following or was refractory to at least two prior induction regimens. A 1,500-mg/m^2 dose of ARRANON was administered by intravenous infusion over 2 hours on Days 1, 3, and 5 repeated every 21 days. Patients who experienced signs or symptoms of Grade 2 or greater neurologic toxicity on therapy were to be discontinued from further therapy with ARRANON. Seventeen patients had a diagnosis of T-ALL and 11 had a diagnosis of T-LBL. For patients with ≥ 2 prior inductions, the age range was 16 to 65 years (mean: 34 years) and most patients were male (82%) and Caucasian (61%). Patients with central nervous system (CNS) disease were not eligible.

Complete response (CR) in this trial was defined as bone marrow blast counts ≤ 5%, no other evidence of disease, and full recovery of peripheral blood counts. Complete response without complete hematologic recovery (CR*) was also assessed. The results of the trial for patients who had received ≥ 2 prior inductions are shown in Table 5.

Table 5. Efficacy Results in Adult Patients With ≥ 2 Prior Inductions Treated With 1,500 mg/m^2 of ARRANON Administered by Intravenous Infusion Over 2 Hours on Days 1, 3, and 5 Repeated Every 21 Days
 | N = 28
CR plus CR* % (n) [95% CI] | 21% (6) [8%, 41%]
CR % (n) [95% CI] | 18% (5) [6%, 37%]
CR* % (n) [95% CI] | 4% (1) [0%, 18%]
Duration of CR plus CR* (range in weeks)a | 4 to 195+
Median overall survival (weeks) [95% CI] | 20.6 weeks [10.4, 36.4]

Abbreviations: CR, complete response; CI, confidence interval;
  CR*, complete response without hematologic recovery.
  a Does not include 1 patient who was transplanted (duration of response was 156+ weeks).

The mean number of days on therapy was 56 days (range of 10 to 136 days). Time to CR plus CR* ranged from 2.9 to 11.7 weeks.

14.2 Pediatric Clinical Trial in Relapsed or Refractory T-ALL and T-LBL

The safety and efficacy of ARRANON in pediatric patients were studied in a clinical trial which included patients age 21 years and younger, who had relapsed or refractory T-ALL or T-LBL. Eighty-four (84) patients, 39 of whom had received two or more prior induction regimens, were treated with 650 mg/m^2/day of ARRANON administered by intravenous infusion over 1 hour daily for 5 consecutive days repeated every 21 days (see Table 6). Patients who experienced signs or symptoms of Grade 2 or greater neurologic toxicity on therapy were to be discontinued from further therapy with ARRANON.

Table 6. Pediatric Clinical Trial - Patient Allocation
Patient Population | N
Patients treated at 650 mg/m^2/day x 5 days, every 21 days | 84
Patients with T-ALL or T-LBL with two or more prior induction treated at 650 mg/m^2/day x 5 days, every 21 days | 39
Patients with T-ALL or T-LBL with one prior induction treated at 650 mg/m^2/day x 5 days, every 21 days | 31
Abbreviations: T-ALL, T-cell acute lymphoblastic leukemia; T-LBL, T-cell lymphoblastic lymphoma.

The 84 patients ranged in age from 2.5 to 21.7 years (overall mean: 11.9 years), 52% were 3 to 12 years of age and most were male (74%) and Caucasian (62%). The majority (77%) of patients had a diagnosis of T-ALL.

Complete response (CR) in this trial was defined as bone marrow blast counts ≤ 5%, no other evidence of disease, and full recovery of peripheral blood counts. Complete response without full hematologic recovery (CR*) was also assessed as a meaningful outcome in this trial. Duration of response is reported from date of response to date of relapse, and may include subsequent stem cell transplant. Efficacy results are presented in Table 7.

Table 7. Efficacy Results in Patients Age 21 Years and Younger at Diagnosis With ≥ 2 Prior Inductions Treated With 650 mg/m^2 of ARRANON Administered by Intravenous Infusion Over 1 Hour Daily for 5 Consecutive Days Repeated Every 21 Days
 | N = 39
CR plus CR* % (n) [95% CI] | 23% (9) [11%, 39%]
CR % (n) [95% CI] | 13% (5) [4%, 27%]
CR* % (n) [95% CI] | 10% (4) [3%, 24%]
Duration of CR plus CR* (range in weeks)a | 3.3 to 9.3
Median overall survival (weeks) [95% CI] | 13.1 [8.7, 17.4]

Abbreviations: CR, complete response; CI, confidence interval;
  CR*, complete response without hematologic recovery.
  a Does not include 5 patients who were transplanted or had subsequent systemic chemotherapy (duration of response in these 5 patients was 4.7 to 42.1 weeks).

The mean number of days on therapy was 46 days (range: 7-129 days). Median time to CR plus CR* was 3.4 weeks (95% CI: 3.0, 3.7).

15 REFERENCES

1. “OSHA Hazardous Drugs.” OSHA. http://www.osha.gov/SLTC/hazardousdrugs/index.html

16 HOW SUPPLIED/STORAGE AND HANDLING

ARRANON (nelarabine) injection is supplied as a clear, colorless, sterile solution in Type I, clear glass single-dose vials with a gray bromobutyl rubber stopper (not made with natural rubber latex) and an aluminum seal with a snap-off cap.

Single-dose Vials are available in 250 mg/50 mL (5 mg/mL) strength and the following carton sizes:

NDC 0078-0683-61 (package of 1). Discard Unused Portion.

NDC 0078-0683-06 (package of 6). Discard Unused Portion.

Store ARRANON (nelarabine) Injection between 20°C and 25°C (68°F and 77°F); excursions permitted to 15°C to 30°C (59°F to 86°F). See USP Controlled Room Temperature.

17 PATIENT COUNSELING INFORMATION

Advise the patient to read the FDA-approved patient labeling (Patient Information).

Hematologic Adverse Reactions

- Advise patients that leukopenia, thrombocytopenia, anemia, and neutropenia, including febrile neutropenia, have been associated with ARRANON.
- Advise patients that complete blood counts, including platelets, will be monitored regularly during treatment [see Warnings and Precautions (5.2), Adverse Reactions (6.1)].

Embryo-Fetal Toxicity

- Advise pregnant females of reproductive potential and males with female partners of reproductive potential of the potential risk to the fetus. Advise females of reproductive potential to use effective contraception during treatment with ARRANON. Instruct females to inform their physician of a known or suspected pregnancy.
- Advise male patients with partners of reproductive potential to use condoms during treatment with ARRANON and for 3 months after the last dose [see Warnings and Precautions (5.3), Use in Specific Populations (8.1, 8.3)].

Tumor Lysis Syndrome

- Advise patients of the risk of tumor lysis syndrome [see Warnings and Precautions (5.4), Adverse Reactions (6.1)].

Vaccinations

- Instruct patients not to receive live vaccines during treatment with ARRANON [see Warnings and Precautions (5.5), Adverse Reactions (6.1)].

Effects on Ability to Drive and Use Machines

- Patients receiving ARRANON may experience somnolence during and for several days after treatment. Instruct patients to not drive or engage in hazardous occupations or activities until somnolence has resolved [see Warnings and Precautions (5.6), Adverse Reactions (6.1)].

Neurologic Adverse Reactions

- Instruct patients to contact their physician if they experience new or worsening symptoms of peripheral neuropathy [see Boxed Warning, Dosage and Administration (2.3), Warnings and Precautions (5.1), Adverse Reactions (6.1)]. These signs and symptoms include: tingling or numbness in fingers, hands, toes, or feet; difficulty with the fine motor coordination tasks such as buttoning clothing; unsteadiness while walking; weakness arising from a low chair; weakness in climbing stairs; increased tripping while walking over uneven surfaces.
- Advise patients of the risk of seizures [see Adverse Reactions (6.1)]. If a seizure occurs, instruct patients to promptly notify the physician administering ARRANON.

Infection

- Instruct patients to promptly notify their physician if they develop fever or signs of infection while on therapy [see Adverse Reactions (6.1, 6.2)].

Lactation

- Advise women not to breastfeed during treatment with ARRANON [see Use in Specific Populations (8.2)].

Distributed by:
Novartis Pharmaceuticals Corporation
East Hanover, New Jersey 07936

© Novartis

PATIENT INFORMATION
ARRANON® (AIR-ra-non)
(nelarabine) Injection

Read the Patient Information that comes with ARRANON before you or your child starts treatment with ARRANON. Read the information you get each time before each treatment with ARRANON. There may be new information. This information does not take the place of talking with the doctor about your or your child’s medical condition or treatment. Talk to your or your child’s doctor, if you have any questions.

What is the most important information I should know about ARRANON?

ARRANON may cause blood related adverse reactions. Your doctor will do blood tests regularly during treatment to monitor blood counts, including platelets.

ARRANON may cause serious nervous system problems including:

- extreme sleepiness
- seizures
- coma
- numbness and tingling in the hands, fingers, feet, or toes (peripheral neuropathy)
- weakness and paralysis

Call the doctor right away if you or your child has the following symptoms:

- seizures
- numbness and tingling in the hands, fingers, feet, or toes
- problems with fine motor skills such as buttoning clothes
- unsteadiness while walking
- increased tripping while walking
- weakness when getting out of a chair or walking upstairs

These symptoms may not go away even when treatment with ARRANON is stopped.

What is ARRANON?

ARRANON is an anti-cancer medicine used to treat adults and children who have:
2. T-cell acute lymphoblastic leukemia (T-ALL)
3. T-cell lymphoblastic lymphoma (T-LBL)

What should you tell the doctor before you or your child starts ARRANON?

Tell the doctor about all health conditions you or your child have, including if you or your child:
2. have any nervous system problems.
3. have kidney problems.
4. are breastfeeding or plan to breastfeed. It is not known whether ARRANON passes through breast milk. You should not breastfeed during treatment with ARRANON.
5. are pregnant or plan to become pregnant. ARRANON can harm your unborn baby. You should not become pregnant while you are taking ARRANON. You should use effective birth control to avoid getting pregnant. Talk with your doctor about your choices.
6. are male (including if you have had a vasectomy) with a sexual partner who is pregnant, think that they may be pregnant, or who could become pregnant. You should use condoms during sexual intercourse during treatment with ARRANON and for 3 months after last dose.
Tell the doctor about all the medicines you or your child take, including prescription and nonprescription medicines, vitamins, and herbal supplements.

How is ARRANON given?

ARRANON is an intravenous medicine. This means it is given through a tube in your vein.

What should you or your child avoid during treatment with ARRANON?

- You or your child should not drive or operate dangerous machines. ARRANON may cause sleepiness during and for several days after treatment.
- You or your child should not receive vaccines made with live germs during treatment with ARRANON.

What are the possible side effects of ARRANON?

ARRANON may cause serious nervous system problems. See “What is the most important information I should know about ARRANON?”

ARRANON may also cause:

- decreased blood counts such as low red blood cells, low white blood cells, and low platelets. Blood tests should be done regularly to check blood counts. Call the doctor right away if you or your child:
  • is more tired than usual, pale, or has trouble breathing
  • has a fever or other signs of an infection
  • bruises easy or has any unusual bleeding
- stomach area problems such as nausea, vomiting, diarrhea, and constipation
- headache
- sleepiness
- blurry eyesight

Call your doctor right away if you experience unexplained muscle pain, tenderness, or weakness while taking ARRANON. This is because on rare occasions, muscle problems can be serious.

These are not all the side effects associated with ARRANON. Ask your doctor or pharmacist for more information.

Call your doctor for medical advice about side effects. You may report side effects to FDA at 1-800-FDA-1088.

General Advice about ARRANON

This leaflet summarizes important information about ARRANON. If you have questions or problems, talk with your or your child’s doctor. You can ask your doctor or pharmacist for information about ARRANON that is written for healthcare providers or it is available at www.pharma.us.novartis.com.

Distributed by:
Novartis Pharmaceuticals Corporation
East Hanover, New Jersey 07936

© Novartis

This Patient Information has been approved by the U.S. Food and Drug Administration. Revised: Mar 2025

PRINCIPAL DISPLAY PANEL

NDC 0078-0683-61 Rx only

ARRANON®
(nelarabine) Injection

250 mg/50 mL
(5 mg/mL)

For Intravenous Infusion Only

One 50 mL Vial

Single-Dose Vial.

Discard Unused Portion.

WARNING: Hazardous Drug

NOVARTIS